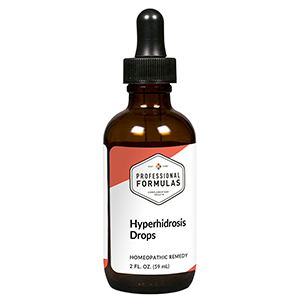 DRUG LABEL: Hyperhidrosis Drops
NDC: 63083-2144 | Form: LIQUID
Manufacturer: Professional Complementary Health Formulas
Category: homeopathic | Type: HUMAN OTC DRUG LABEL
Date: 20190815

ACTIVE INGREDIENTS: ACETIC ACID 6 [hp_X]/59 mL; LIQUID PETROLEUM 6 [hp_X]/59 mL; SAMBUCUS NIGRA FLOWERING TOP 6 [hp_X]/59 mL; GRAPHITE 12 [hp_X]/59 mL; PHOSPHORIC ACID 12 [hp_X]/59 mL; SEPIA OFFICINALIS JUICE 12 [hp_X]/59 mL; VERATRUM ALBUM ROOT 12 [hp_X]/59 mL; OYSTER SHELL CALCIUM CARBONATE, CRUDE 30 [hp_X]/59 mL; ACTIVATED CHARCOAL 30 [hp_X]/59 mL; MERCURIUS SOLUBILIS 30 [hp_X]/59 mL
INACTIVE INGREDIENTS: ALCOHOL; WATER

C144

ACTIVE INGREDIENTS

Aceticum acidum 6X
Petroleum 6X
Sambucus nigra 6X
Graphites 12X
Phosphoricum acidum 12X
Sepia 12X
Veratrum album 12X
Calcarea carbonica 30X
Carbo vegetabilis 30X
Mercurius solubilis 30X

QUESTIONS

Professional Formulas

PO Box 2034 Lake Oswego, OR 97035

INDICATIONS

For the temporary relief of excessive sweating.*

PURPOSE

*Claims based on traditional homeopathic practice, not accepted medical evidence. Not FDA evaluated.

WARNINGS

Consult a doctor if condition worsens or if symptoms persist. Keep out of the reach of children. In case of overdose, get medical help or contact a poison control center right away. If pregnant or breastfeeding, ask a healthcare professional before use.

Keep out of the reach of children.

PREGNANCY OR BREAST FEEDING

If pregnant or breastfeeding, ask a healthcare professional before use.

DIRECTIONS

Place drops under tongue 30 minutes before/after meals. Adults and children 12 years and over: Take 10 drops up to 3 times per day for up to 6 weeks. For immediate onset of symptoms, take 10 to 15 drops every 15 minutes up to 3 hours. For less severe symptoms, take 10-15 drops hourly up to 8 hours. Consult a physician for use in children under 12 years of age.

OTHER INFORMATION

Tamper resistant. If seal is broken, do not use. After opening, close container tightly and store at room temperature away from heat.

INACTIVE INGREDIENTS

20% ethanol, purified water.

LABEL

Est 1985

Professional Formulas

Complementary Health

Hyperhidrosis Drops

Homeopathic Remedy

2 FL. OZ. (59 mL)